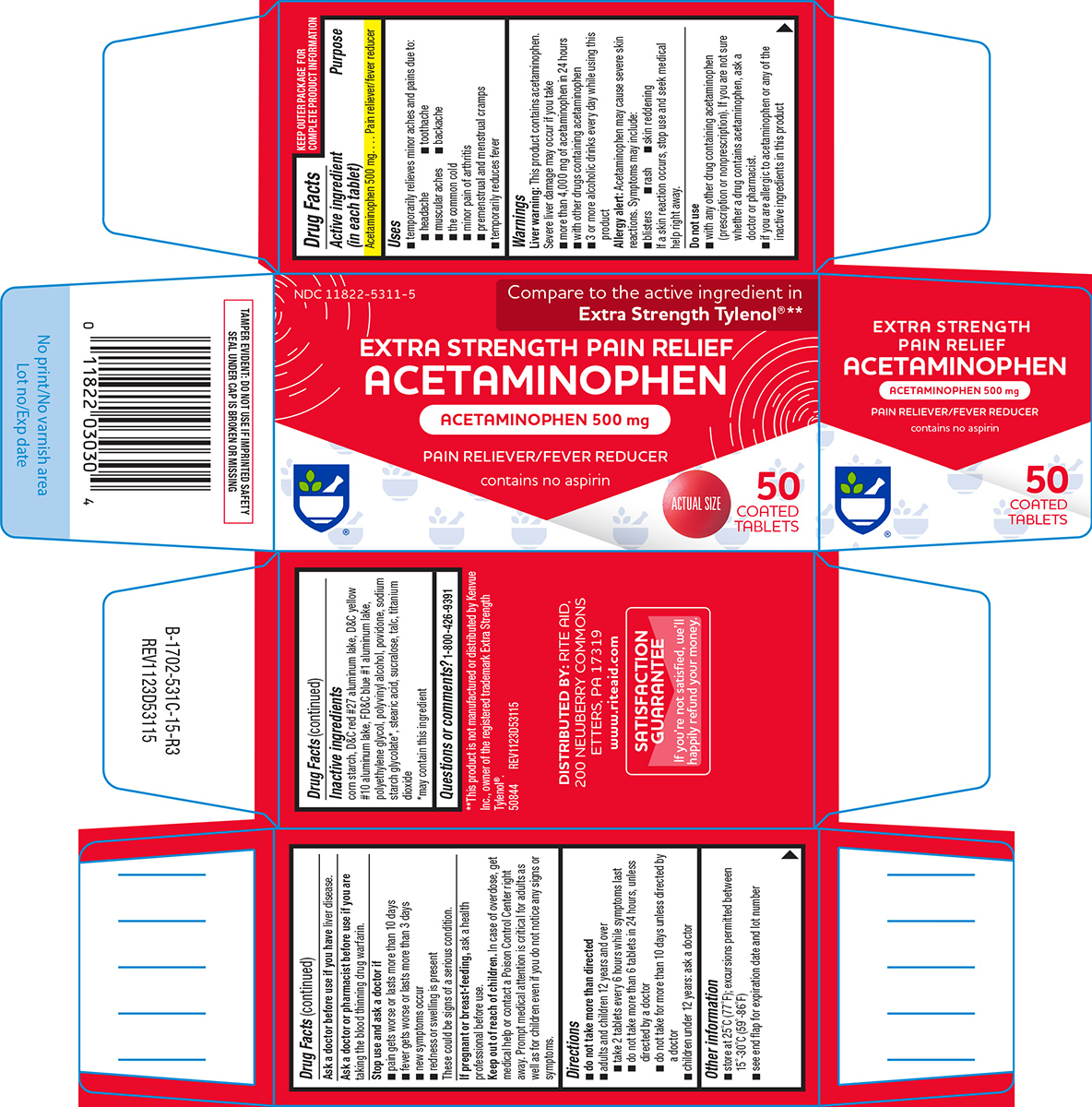 DRUG LABEL: Extra Strength pain relief
NDC: 11822-5311 | Form: TABLET, FILM COATED
Manufacturer: Rite Aid Corporation
Category: otc | Type: HUMAN OTC DRUG LABEL
Date: 20250917

ACTIVE INGREDIENTS: ACETAMINOPHEN 500 mg/1 1
INACTIVE INGREDIENTS: STARCH, CORN; D&C RED NO. 27 ALUMINUM LAKE; D&C YELLOW NO. 10 ALUMINUM LAKE; FD&C BLUE NO. 1 ALUMINUM LAKE; POLYETHYLENE GLYCOL, UNSPECIFIED; POLYVINYL ALCOHOL, UNSPECIFIED; POVIDONE, UNSPECIFIED; STEARIC ACID; SUCRALOSE; TALC; TITANIUM DIOXIDE

Rite Aid 44-531C

Active ingredient (in each tablet)

Acetaminophen 500 mg

Purpose

Pain reliever/fever reducer

Uses

- temporarily relieves minor aches and pains due to:
  - headache
  - toothache
  - the common cold
  - muscular aches
  - backache
  - minor pain of arthritis
  - premenstrual and menstrual cramps
- temporarily reduces fever

Warnings

Liver warning: This product contains acetaminophen. Severe liver damage may occur if you take

- more than 4,000 mg of acetaminophen in 24 hours
- with other drugs containing acetaminophen
- 3 or more alcoholic drinks every day while using this product

Allergy alert: Acetaminophen may cause severe skin reactions. Symptoms may include:

- blisters
- rash
- skin reddening

If a skin reaction occurs, stop use and seek medical help right away.

Do not use

- with any other drug containing acetaminophen (prescription or nonprescription). If you are not sure whether a drug contains acetaminophen, ask a doctor or pharmacist.
- if you are allergic to acetaminophen or any of the inactive ingredients in this product

Ask a doctor before use if you have

liver disease.

Ask a doctor or pharmacist before use if you are

taking the blood thinning drug warfarin.

Stop use and ask a doctor if

- pain gets worse or lasts more than 10 days
- fever gets worse or lasts more than 3 days
- new symptoms occur
- redness or swelling is present

These could be signs of a serious condition.

If pregnant or breast-feeding,

ask a health professional before use.

Keep out of reach of children.

In case of overdose, get medical help or contact a Poison Control Center right away. Prompt medical attention is critical for adults as well as for children even if you do not notice any signs or symptoms.

Directions

- do not take more than directed
- adults and children 12 years and over
  - take 2 tablets every 6 hours while symptoms last
  - do not take more than 6 tablets in 24 hours, unless directed by a doctor
  - do not take for more than 10 days unless directed by a doctor
- children under 12 years: ask a doctor

Other information

- store at 25°C (77°F); excursions permitted between 15°-30°C (59°-86°F)
- see end flap for expiration date and lot number

Inactive ingredients

corn starch, D&C red #27 aluminum lake, D&C yellow #10 aluminum lake, FD&C blue #1 aluminum lake, polyethylene glycol, polyvinyl alcohol, povidone, sodium starch glycolate*, stearic acid, sucralose, talc, titanium dioxide
*may contain this ingredient

Questions or comments?

1-800-426-9391

Principal display panel

NDC 11822-5311-5

Compare to the active ingredient in
Extra Strength Tylenol® **

EXTRA STRENGTH PAIN RELIEF
ACETAMINOPHEN

ACETAMINOPHEN 500 mg
PAIN RELIEVER/FEVER REDUCER

contains no aspirin

50
COATED
TABLETS

ACTUAL SIZE

**This product is not manufactured or distributed by Kenvue
Inc., owner of the registered trademark Extra Strength
Tylenol®.

50844 REV1123D53115

TAMPER EVIDENT: DO NOT USE IF IMPRINTED SAFETY
SEAL UNDER CAP IS BROKEN OR MISSING

DISTRIBUTED BY: RITE AID,
200 NEWBERRY COMMONS
ETTERS, PA 17319
www.riteaid.com

SATISFACTION
GUARANTEE
If you're not satisfied, we'll
happily refund your money.

Rite Aid 44-531C